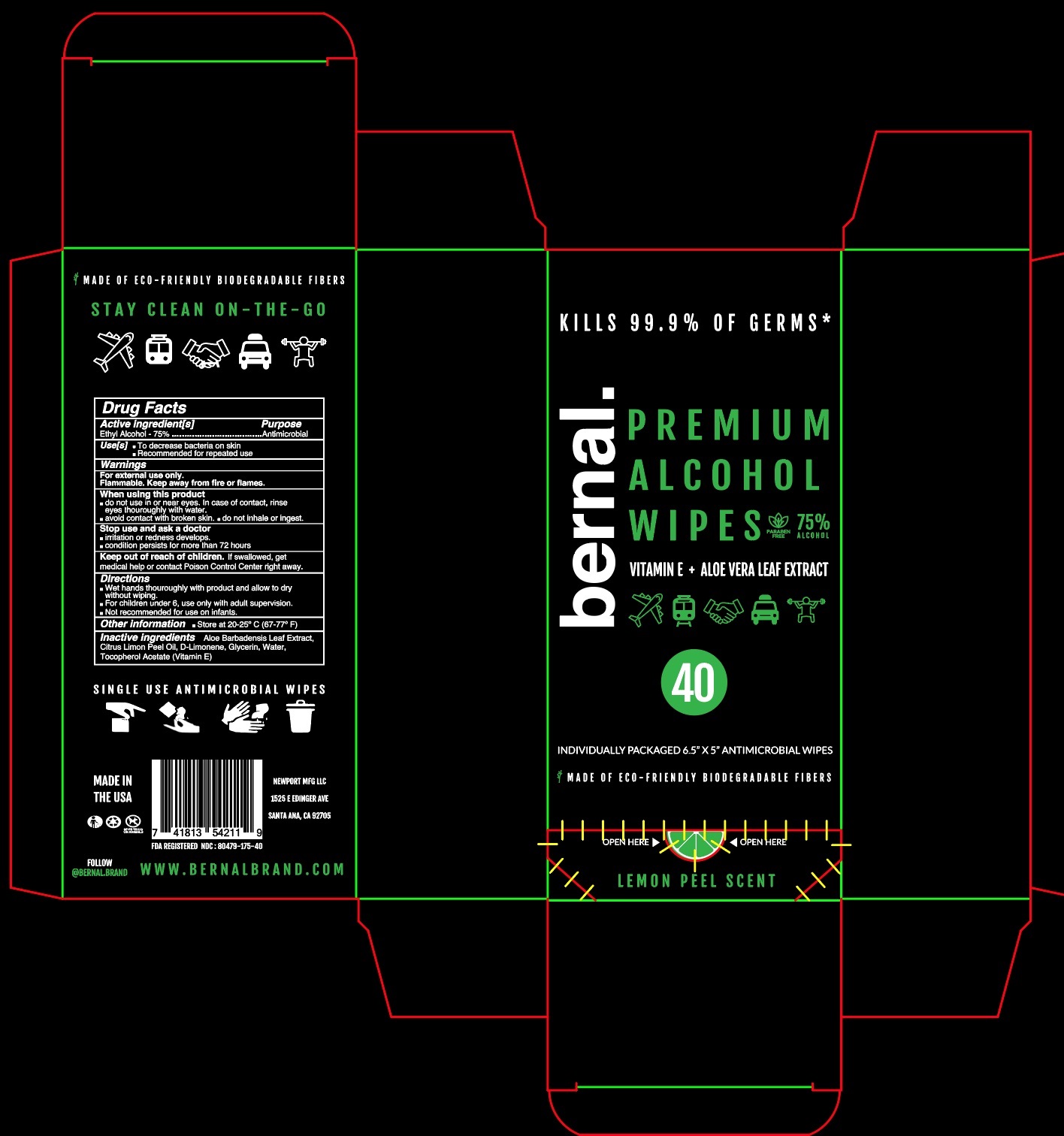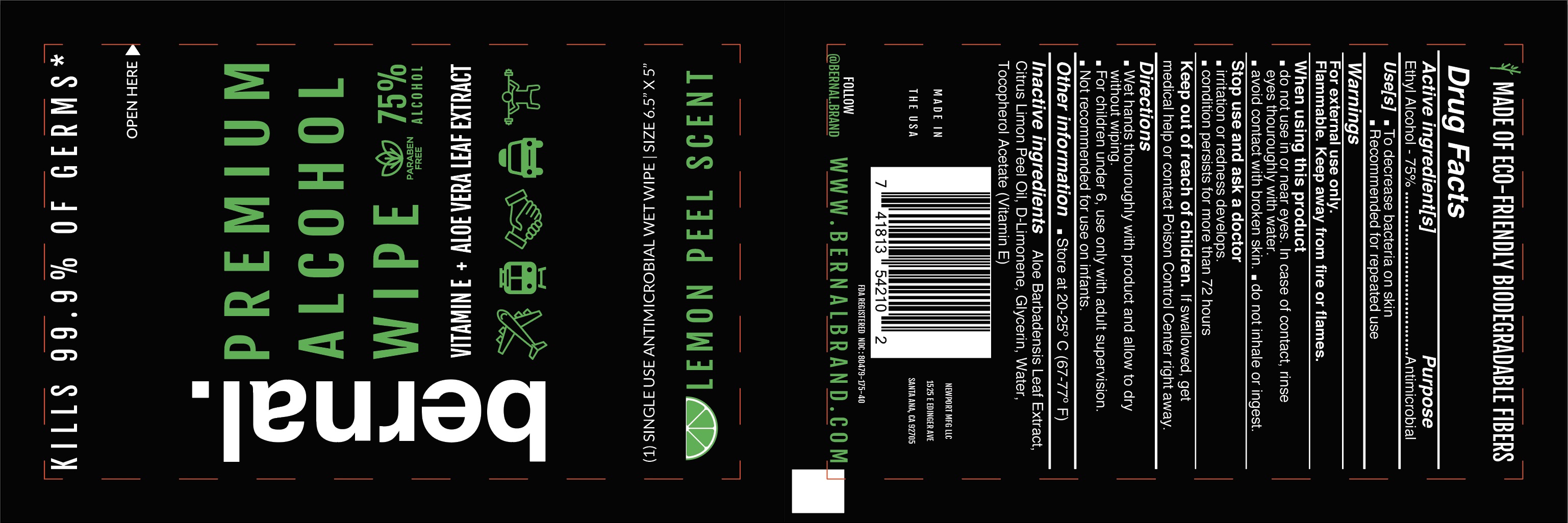 DRUG LABEL: Bernal Premium Alcohol Wipe
NDC: 80479-175 | Form: CLOTH
Manufacturer: Newport MFG LLC
Category: otc | Type: HUMAN OTC DRUG LABEL
Date: 20201021

ACTIVE INGREDIENTS: ALCOHOL 75 mL/100 mL
INACTIVE INGREDIENTS: LIMONENE, (+)-; .ALPHA.-TOCOPHEROL ACETATE; ALOE VERA LEAF; GLYCERIN; LEMON OIL; WATER

Bernal Premium Alcohol Wipe

Active Ingredient(s)

Ethyl Alcohol 75% v/v. Purpose: Antimicrobial

Purpose

Antimicrobial

Use

- to decrease bacteria on skin
- recommended for repeated use

Warnings

For external use only. Flammable. Keep away from heat or flame

Do not use

- in children less than 2 months of age
- on open skin wounds

- Do not use in or near eyes. In case of contact, rinse eyes thoroughly with water.
- Avoid contact with broken skin
- Do not inhale or ingest

STOP USE

- Irritation or redness develops.
- Condition persists for more than 72 hours

Keep out of reach of children. If swallowed, get medical help or contact a Poison Control Center right away.

Directions

- Wet hands thoroughly with product and allow drying without wiping.
- For children under 6, use only with adult supervision.
- Not recommended for use on infants.

Other information

- Store between 20-25C (67-77F)

Inactive ingredients

Aloe Barbadensis Leaf Extract, Citrus Limon Peel Oil, D-Limonene, Glycerin, Tocopherol Acetate (Vitamin E), Water

Package Label - Principal Display Panel

3 mL NDC: 80479-175-40